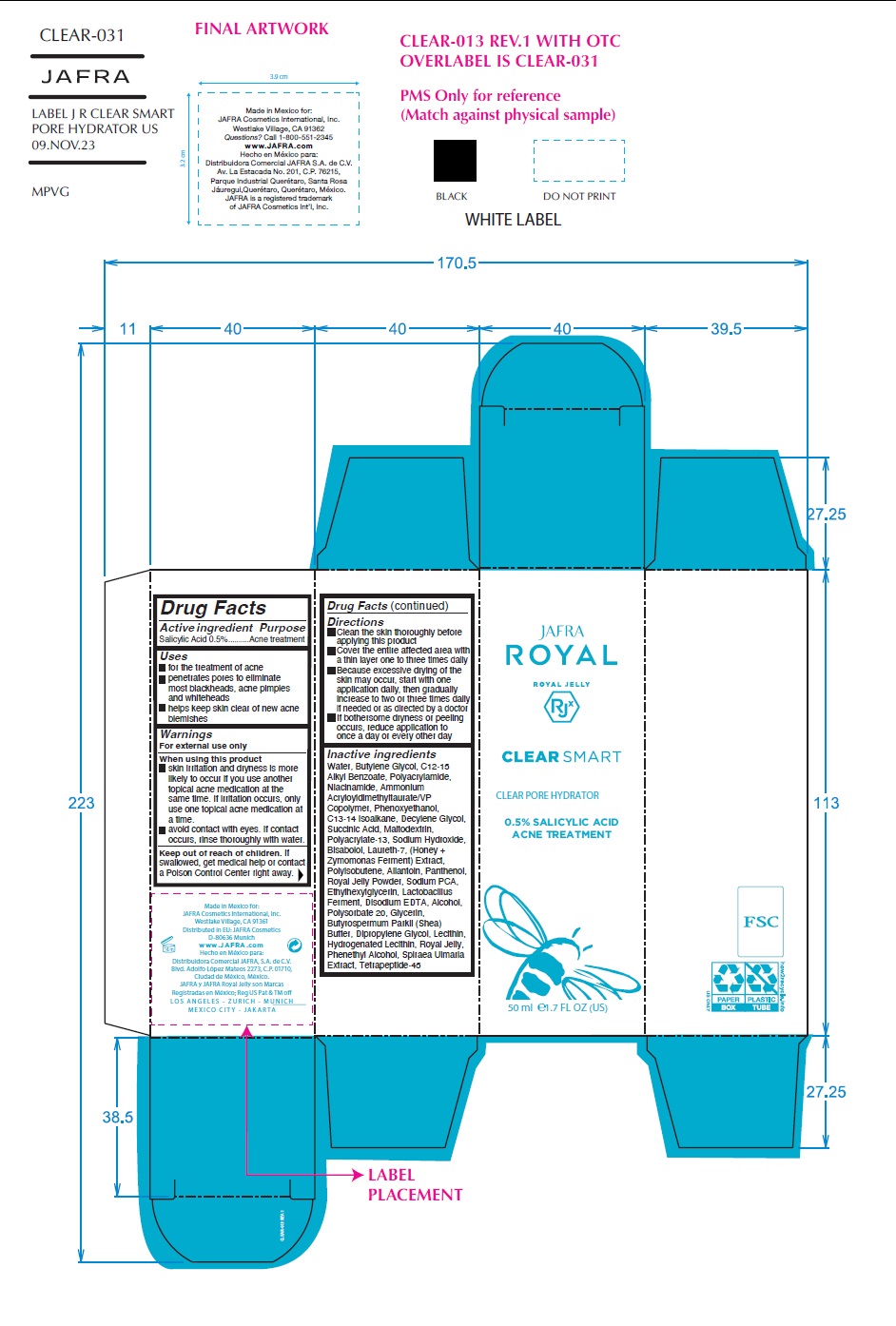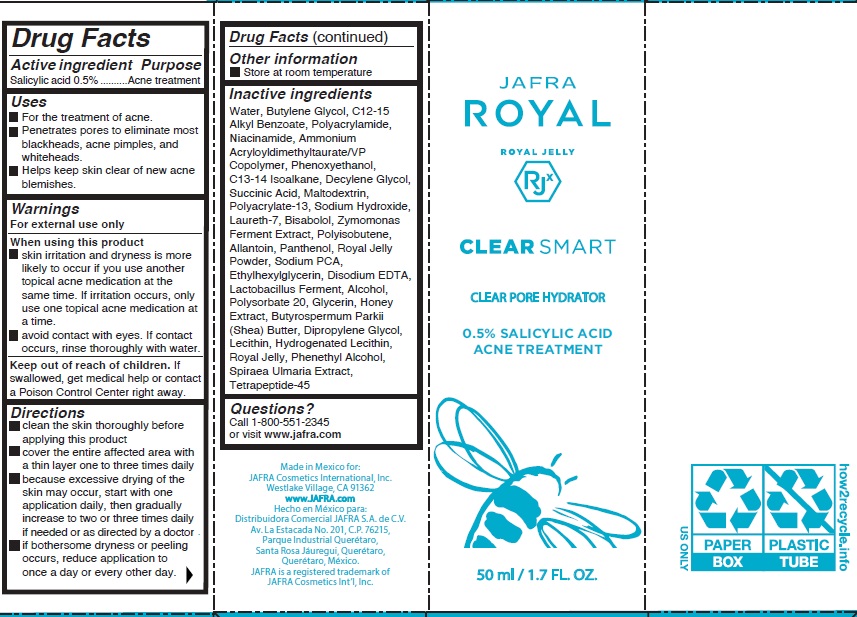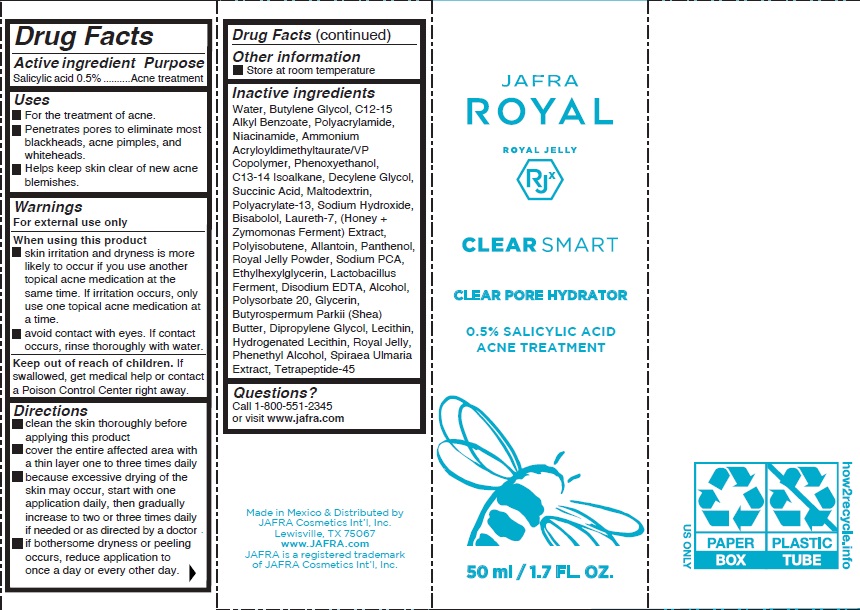 DRUG LABEL: Clear Smart Clear Pore Hydrator
NDC: 68828-701 | Form: GEL
Manufacturer: Distribuidora Comercial Jafra, S.A. de C.V.
Category: otc | Type: HUMAN OTC DRUG LABEL
Date: 20251021

ACTIVE INGREDIENTS: SALICYLIC ACID 0.5 g/100 mL
INACTIVE INGREDIENTS: DECYLENE GLYCOL; PHENYLETHYL ALCOHOL; MALTODEXTRIN; SODIUM HYDROXIDE; PANTHENOL; HYDROGENATED SOYBEAN LECITHIN; HONEY; POLYACRYLAMIDE (1500 MW); ROYAL JELLY; SODIUM PYRROLIDONE CARBOXYLATE; SHEA BUTTER; C13-14 ISOPARAFFIN; SUCCINIC ACID; WATER; ALKYL (C12-15) BENZOATE; AMMONIUM ACRYLOYLDIMETHYLTAURATE/VP COPOLYMER; NIACINAMIDE; ALLANTOIN; DIPROPYLENE GLYCOL; LECITHIN, SOYBEAN; EDETATE DISODIUM; LAURETH-7; PHENOXYETHANOL; ETHYLHEXYLGLYCERIN; GLYCERIN; LEVOMENOL; BUTYLENE GLYCOL; FILIPENDULA ULMARIA ROOT; ALCOHOL; POLYSORBATE 20; POLYISOBUTYLENE (1300 MW); LIMOSILACTOBACILLUS FERMENTUM; POLYACRYLATE-13

Clear Smart Clear Pore Hydrator

Active ingredient

Salicylic Acid 0.5%

Purpose

Acne treatment

Uses

● For the treatment of acne.
● Penetrates pores to eliminate most blackheads, acne pimples, and whiteheads.
● Helps keep skin clear of new acne blemishes.

Warnings

For external use only

When using this product

- skin irritation and dryness is more likely to occur if you use another topical acne medication at the same time. If irritation occurs, only use one topical acne medication at a time.
- avoid contact with eyes. If contact occurs, rinse thoroughly with water.

Keep out of reach of children.If swallowed, get medical help or contact a Poison Control Center right away.

Directions

- Clean the skin thoroughly before applying
- Cover the entire affected area with a thin layer one to three times daily
- Because excessive drying of the skin may occur, start with one application daily, then gradually increase to two or three times daily if needed or as directed by a doctor
- If bothersome dryness or peeling occurs, reduce application to once a day or every other day.

Other information

• Store at room temperature

Inactive ingredients

Water, Butylene Glycol, C12-15 Alkyl Benzoate, Polyacrylamide, Niacinamide, Ammonium Acryloyldimethyltaurate/VP Copolymer, Phenoxyethanol, C13-14 Isoalkane, Decylene Glycol, Succinic Acid, Maltodextrin, Polyacrylate-13, Sodium Hydroxide, Bisabolol, Laureth-7, (Honey + Zymomonas Ferment) Extract, Polyisobutene, Allantoin, Panthenol, Royal Jelly Powder, Sodium PCA, Ethylhexylglycerin, Lactobacillus Ferment, Disodium EDTA, Alcohol, Polysorbate 20, Glycerin, Butyrospermum Parkii (Shea) Butter, Dipropylene Glycol, Lecithin, Hydrogenated Lecithin, Royal Jelly, Phenethyl Alcohol, Spiraea Ulmaria Extract, Tetrapeptide-45

Questions?Call 1-800-551-2345 or visit www.jafra.com